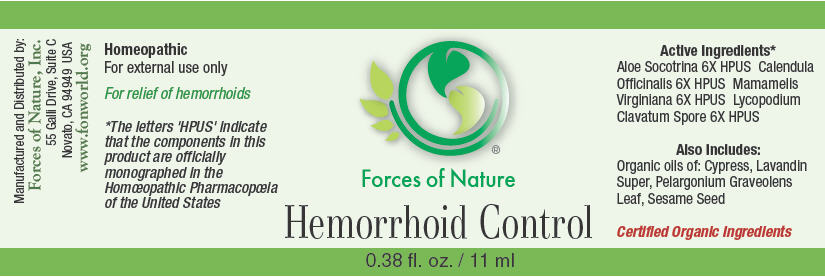 DRUG LABEL: Hemorrhoid Control
NDC: 51393-6444 | Form: SOLUTION/ DROPS
Manufacturer: Forces of Nature
Category: homeopathic | Type: HUMAN OTC DRUG LABEL
Date: 20100824

ACTIVE INGREDIENTS: Aloe 6 [hp_X]/1000 mL; CALENDULA OFFICINALIS FLOWERING TOP 6 [hp_X]/1000 mL; HAMAMELIS VIRGINIANA ROOT BARK/STEM BARK 6 [hp_X]/1000 mL; Lycopodium clavatum Spore 6 [hp_X]/1000 mL

Hemorrhoid Control

Drug Facts

Indications

For relief for hemorrhoids

ACTIVE INGREDIENT

PURPOSE

Homeopathic Active Ingredients [The letters 'HPUS' indicate that the components in this product are officially monographed in the Homœopathic Pharmacopœia of the United States.]
Equal parts of: | Purpose
Aloe 6X HPUS | Relief for hemorrhoids that are tender, sore, burning
Calendula Officinalis 6X HPUS | Promotes healthy skin and healing
Mamamelis Virginiana 6X HPUS | Relief of hemorrhoids that are sore or burning
Lycopodium Clavatum Spore 6X HPUS | Relief for painful hemorrhoids

Also Contains Certified Organic

Cypress Oil, Lavandin Super Oil, Pelargonium Graveolens Leaf Oil, Sesame Seed Oil

Directions

Moisten cotton ball with water, apply 2-3 drops of product. Dab onto treatment area 2-4 times per day until problem is gone.

Warnings

Some individuals may be sensitive to essential oils.Begin with a small drop to determine if the product causes any increased redness or irritation and discontinue use if it irritates your skin.

PREGNANCY OR BREAST FEEDING

If you are pregnant or breast-feeding, ask a health professional before use.

WHEN USING

For external use only. If accidental ingestion, get medical help or contact a Poison Control Center. Do not apply to the eyes; in the event of contact, flush with water and seek advice from medical personnel.

KEEP OUT OF REACH OF CHILDREN

Not to be used with children under 2 years of age. Keep all medicines out of the reach of children.

Stop use and ask a doctor if condition worsens, symptoms last more than 7 days, or clear up and occur again within a few days.

Manufactured by:
Forces of Nature, Inc.
55 Galli Drive, Suite C
Novato, CA 94949 USA
www.fonworld.org

Product questions?

877-975-3797

NDC#: 51393-6444-1 (11ml) // 51393-6444-2 (33ml)

Principal Display Panel - 11 ml Bottle Label

Forces of Nature

Hemorrhoid Control

0.38 fl. oz. / 11 ml